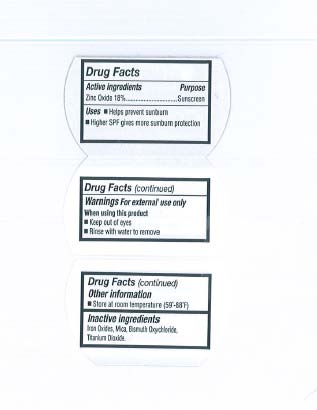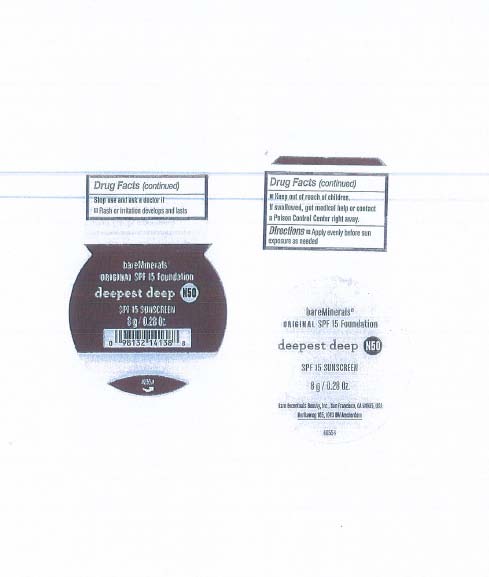 DRUG LABEL: Deepest Deep
NDC: 98132-887 | Form: POWDER
Manufacturer: Bare Escentuals Beauty Inc.
Category: otc | Type: HUMAN OTC DRUG LABEL
Date: 20120614

ACTIVE INGREDIENTS: Zinc Oxide 18 g/100 g
INACTIVE INGREDIENTS: MICA; BISMUTH OXYCHLORIDE; BROWN IRON OXIDE; FERROSOFERRIC OXIDE; FERRIC OXIDE YELLOW; TITANIUM DIOXIDE

Bare Minerals Original SPF 15 Foundation Deepest Deep

Active Ingredients

Zinc Oxide 18%

Purpose

Sunscreen

Indication & Usage

- Helps prevent sunburn
- Higher SPF gives more sunburn protection

Warnings

For External use only

When using this product

- Keep out of eyes
- Rinse with water to remove

Stop use and ask a doctor if

Rash or irritation develops and lasts

Keep out of children.

If swallowed, get medical help or contact a Poison Control Center right away.

Directions

Apply evenly before sun exposure as needed